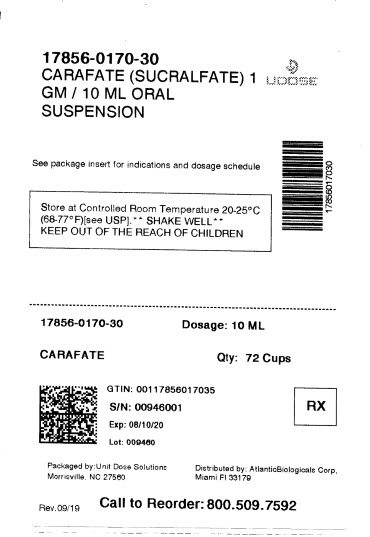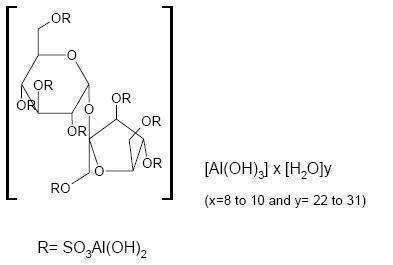 DRUG LABEL: Carafate
NDC: 17856-0170 | Form: SUSPENSION
Manufacturer: ATLANTIC BIOLOGICALS CORP.
Category: prescription | Type: HUMAN PRESCRIPTION DRUG LABEL
Date: 20210126

ACTIVE INGREDIENTS: Sucralfate 1 g/10 mL
INACTIVE INGREDIENTS: FD&C RED NO. 40 0.004 mg/10 mL; Glycerin 87.92 mg/10 mL; Methylparaben 1.78 mg/10 mL; Sorbitol 177.62 mg/10 mL; Water 618.006 mg/10 mL

CARAFATE (sucralfate) Suspension

DESCRIPTION

CARAFATE Suspension contains sucralfate and sucralfate is an α-D-glucopyranoside, β-D-fructofuranosyl-, octakis-(hydrogen sulfate), aluminum complex.

CARAFATE Suspension for oral administration contains 1 g of sucralfate per 10 mL.

CARAFATE Suspension also contains: colloidal silicon dioxide NF, FD&C Red #40, flavor, glycerin USP, methylcellulose USP, methylparaben NF, microcrystalline cellulose NF, purified water USP, simethicone USP, and sorbitol solution USP. Therapeutic category: antiulcer.

CLINICAL PHARMACOLOGY

Sucralfate is only minimally absorbed from the gastrointestinal tract. The small amounts of the sulfated disaccharide that are absorbed are excreted primarily in the urine.

Although the mechanism of sucralfate’s ability to accelerate healing of duodenal ulcers remains to be fully defined, it is known that it exerts its effect through a local, rather than systemic, action. The following observations also appear pertinent:

1. Studies in human subjects and with animal models of ulcer disease have shown that sucralfate forms an ulcer-adherent complex with proteinaceous exudate at the ulcer site.
2. In vitro, a sucralfate-albumin film provides a barrier to diffusion of hydrogen ions.
3. In human subjects, sucralfate given in doses recommended for ulcer therapy inhibits pepsin activity in gastric juice by 32%.
4. In vitro, sucralfate adsorbs bile salts.

These observations suggest that sucralfate’s antiulcer activity is the result of formation of an ulcer-adherent complex that covers the ulcer site and protects it against further attack by acid, pepsin, and bile salts. There are approximately 14 to 16 mEq of acid-neutralizing capacity per 1 g dose of sucralfate.

CLINICAL TRIALS

In a multicenter, double-blind, placebo-controlled study of CARAFATE Suspension, a dosage regimen of 1 g (10 mL) four times daily was demonstrated to be superior to placebo in ulcer healing.
Results From Clinical Trials Healing Rates for Acute Duodenal Ulcer

*P=0.016
†P=0.001
‡P=0.0001
Treatment n Week 2 Healing Rates Week 4 Healing Rates Week 8 Healing Rates
CARAFATE Suspension 145 23(16%) * 66(46%) † 95(66%) ‡
Placebo 147 10(7%) 39(27%) 58(39%)

Equivalence of sucralfate suspension to sucralfate tablets has not been demonstrated.

INDICATIONS AND USAGE

CARAFATE (sucralfate) Suspension is indicated in the short-term (up to 8 weeks) treatment of active duodenal ulcer.

CONTRAINDICATIONS

CARAFATE is contraindicated for patients with known hypersensitivity reactions to the active substance or to any of the excipients.

PRECAUTIONS

The physician should read the "PRECAUTIONS" section when considering the use of CARAFATE in pregnant or pediatric patients, or patients of childbearing potential.

Duodenal ulcer is a chronic, recurrent disease. While short-term treatment with sucralfate can result in complete healing of the ulcer, a successful course of treatment with sucralfate should not be expected to alter the post healing frequency or severity of duodenal ulceration.

Episodes of hyperglycemia have been reported in diabetic patients. Close monitoring of glycemia in diabetic patients treated with sucralfate suspension is recommended. Adjustment of the anti-diabetic treatment dose during the use of sucralfate suspension might be necessary.

Special Populations: Chronic Renal Failure and Dialysis Patients

When sucralfate is administered orally, small amounts of aluminum are absorbed from the gastrointestinal tract. Concomitant use of sucralfate with other products that contain aluminum, such as aluminum-containing antacids, may increase the total body burden of aluminum. Patients with normal renal function receiving the recommended doses of sucralfate and aluminum-containing products adequately excrete aluminum in the urine. Patients with chronic renal failure or those receiving dialysis have impaired excretion of absorbed aluminum. In addition, aluminum does not cross dialysis membranes because it is bound to albumin and transferrin plasma proteins. Aluminum accumulation and toxicity (aluminum osteodystrophy, osteomalacia, encephalopathy) have been described in patients with renal impairment. Sucralfate should be used with caution in patients with chronic renal failure.

Drug Interactions

Some studies have shown that simultaneous sucralfate administration in healthy volunteers reduced the extent of absorption (bioavailability) of single doses of the following: cimetidine, digoxin, fluoroquinolone antibiotics, ketoconazole, l-thyroxine, phenytoin, quinidine, ranitidine, tetracycline, and theophylline. Subtherapeutic prothrombin times with concomitant warfarin and sucralfate therapy have been reported in spontaneous and published case reports. However, two clinical studies have demonstrated no change in either serum warfarin concentration or prothrombin time with the addition of sucralfate to chronic warfarin therapy.

The mechanism of these interactions appears to be nonsystemic in nature, presumably resulting from sucralfate binding to the concomitant agent in the gastrointestinal tract. In all cases studied to date (cimetidine, ciprofloxacin, digoxin, norfloxacin, ofloxacin, and ranitidine), dosing the concomitant medication 2 hours before sucralfate eliminated the interaction. Due to CARAFATE's potential to alter the absorption of some drugs, CARAFATE should be administered separately from other drugs when alterations in bioavailability are felt to be critical. In these cases, patients should be monitored appropriately.

Carcinogenesis, Mutagenesis, Impairment of Fertility

Chronic oral toxicity studies of 24 months’ duration were conducted in mice and rats at doses up to 1 g/kg (12 times the human dose).

There was no evidence of drug-related tumorigenicity. A reproduction study in rats at doses up to 38 times the human dose did not reveal any indication of fertility impairment. Mutagenicity studies were not conducted.

Pregnancy

Teratogenic effects. Pregnancy Category B.

Teratogenicity studies have been performed in mice, rats, and rabbits at doses up to 50 times the human dose and have revealed no evidence of harm to the fetus due to sucralfate. There are, however, no adequate and well-controlled studies in pregnant women. Because animal reproduction studies are not always predictive of human response, this drug should be used during pregnancy only if clearly needed.

Nursing Mothers

It is not known whether this drug is excreted in human milk. Because many drugs are excreted in human milk, caution should be exercised when sucralfate is administered to a nursing woman.

Pediatric Use

Safety and effectiveness in pediatric patients have not been established.

Geriatric Use

Clinical studies of CARAFATE Suspension did not include sufficient numbers of subjects aged 65 and over to determine whether they respond differently from younger subjects. Other reported clinical experience has not identified differences in responses between the elderly and younger patients. In general, dose selection for an elderly patient should be cautious, usually starting at the low end of the dosing range, reflecting the greater frequency of decreased hepatic, renal, or cardiac function, and of concomitant disease or other drug therapy. (See) DOSAGE AND ADMINISTRATION

This drug is known to be substantially excreted by the kidney, and the risk of toxic reactions to this drug may be greater in patients with impaired renal function (See). Because elderly patients are more likely to have decreased renal function, care should be taken in dose selection, and it may be useful to monitor renal function. PRECAUTIONS Special Populations: Chronic Renal Failure and Dialysis Patients

ADVERSE REACTIONS

Adverse reactions to sucralfate tablets in clinical trials were minor and only rarely led to discontinuation of the drug. In studies involving over 2700 patients treated with sucralfate, adverse effects were reported in 129 (4.7%).

Constipation was the most frequent complaint (2%). Other adverse effects reported in less than 0.5% of the patients are listed below by body system:

diarrhea, dry mouth, flatulence, gastric discomfort, indigestion, nausea, vomiting Gastrointestinal:

pruritus, rash Dermatological:

dizziness, insomnia, sleepiness, vertigo Nervous System:

back pain, headache Other:

cases of hypersensitivity have been reported with the use of sucralfate suspension, including anaphylactic reactions, dyspnea, lip swelling, edema of the mouth, pharyngeal edema, pruritus, rash, swelling of the face and urticaria. Post-marketing

Cases of bronchospasm, laryngeal edema and respiratory tract edema have been reported with an unknown oral formulation of sucralfate.

Cases of hyperglycemia have been reported with sucralfate

Bezoars have been reported in patients treated with sucralfate. The majority of patients had underlying medical conditions that may predispose to bezoar formation (such as delayed gastric emptying) or were receiving concomitant enteral tube feedings.

Inadvertent injection of insoluble sucralfate and its insoluble excipients has led to fatal complications, including pulmonary and cerebral emboli. Sucralfate is intended for intravenous administration. not

OVERDOSAGE

Due to limited experience in humans with overdosage of sucralfate, no specific treatment recommendations can be given. Acute oral studies in animals, however, using doses up to 12 g/kg body weight, could not find a lethal dose. Sucralfate is only minimally absorbed from the gastrointestinal tract. Risks associated with acute overdosage should, therefore, be minimal. In rare reports describing sucralfate overdose, most patients remained asymptomatic. Those few reports where adverse events were described included symptoms of dyspepsia, abdominal pain, nausea, and vomiting.

DOSAGE AND ADMINISTRATION

The recommended adult oral dosage for duodenal ulcer is 1 g (10 mL/2 teaspoons) four times per day. CARAFATE should be administered on an empty stomach. Active Duodenal Ulcer.

Antacids may be prescribed as needed for relief of pain but should not be taken within one-half hour before or after sucralfate.

While healing with sucralfate may occur during the first week or two, treatment should be continued for 4 to 8 weeks unless healing has been demonstrated by x-ray or endoscopic examination.

In general, dose selection for an elderly patient should be cautious, usually starting at the low end of the dosing range, reflecting the greater frequency of decreased hepatic, renal, or cardiac function, and of concomitant disease or other drug therapy (See). Elderly: PRECAUTIONS Geriatric Use

Call your doctor for medical advice about side effects. You may report side effects to Aptalis Pharma US, Inc. at 1-800-472-2634 or FDA at 1-800-FDA-1088 or www.fda.gov/medwatch

HOW SUPPLIED

NDC:17856-0170-1 in a CUP of 10 SUSPENSIONS